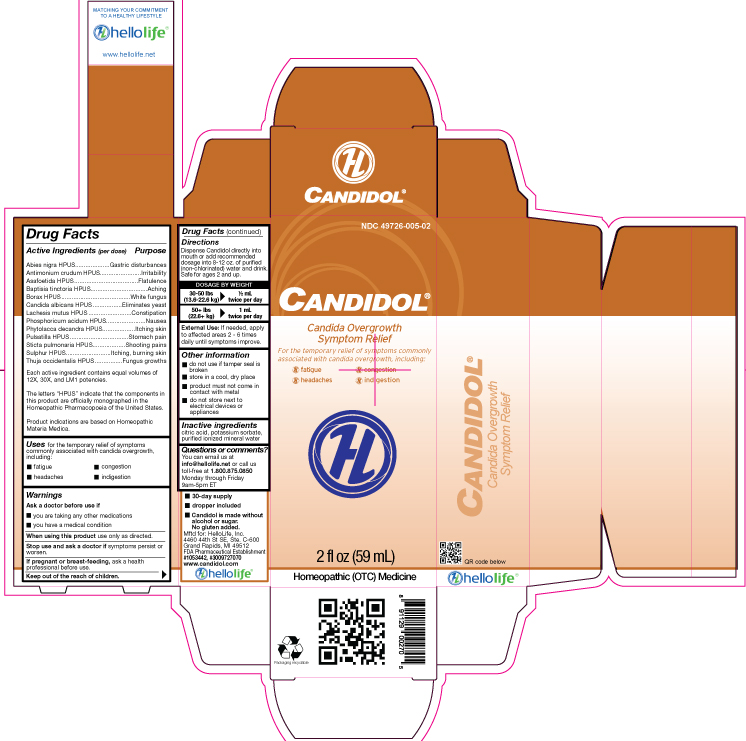 DRUG LABEL: Candidol
NDC: 49726-005 | Form: LIQUID
Manufacturer: Hello Life, Inc.
Category: homeopathic | Type: HUMAN OTC DRUG LABEL
Date: 20181226

ACTIVE INGREDIENTS: PICEA MARIANA RESIN 12 [hp_X]/59 mL; ANTIMONY TRISULFIDE 12 [hp_X]/59 mL; ASAFETIDA 12 [hp_X]/59 mL; BAPTISIA TINCTORIA 12 [hp_X]/59 mL; SODIUM BORATE 12 [hp_X]/59 mL; CANDIDA ALBICANS 12 [hp_X]/59 mL; LACHESIS MUTA VENOM 12 [hp_X]/59 mL; PHOSPHORIC ACID 12 [hp_X]/59 mL; PHYTOLACCA AMERICANA ROOT 12 [hp_X]/59 mL; PULSATILLA VULGARIS 12 [hp_X]/59 mL; LOBARIA PULMONARIA 12 [hp_X]/59 mL; SULFUR 12 [hp_X]/59 mL; THUJA OCCIDENTALIS LEAFY TWIG 12 [hp_X]/59 mL
INACTIVE INGREDIENTS: WATER; POTASSIUM SORBATE; CITRIC ACID MONOHYDRATE

Drug Facts

Active Ingredients (per dose)

Abies nigra HPUS
Antimonium crudum HPUS
Asafoetida HPUS
Baptisia tinctoria HPUS
Borax HPUS
Candida albicans HPUS
Lachesis mutus HPUS
Phosphoricum acidum HPUS
Phytolacca decandra HPUS
Pulsatilla HPUS
Sticta pulmonaria HPUS
Sulphur HPUS
Thuja occidentalis HPUS
Each ingredient contains equal volumes of 12X, 30X, and LM1 potencies.
The letters “HPUS” indicate that the components in this product are officially monographed in the Homeopathic Pharmacopoeia of the United States.
Product indications are based on Homeopathic Materia Medica.

Purpose

Abies nigra HPUS……………………………Gastric disturbances
Antimonium crudum HPUS………………....Irritability
Asafoetida HPUS…………………………….Flatulence
Baptisia tinctoria HPUS……………………..Aching
Borax HPUS…………………………………..White fungus
Candida albicans HPUS……………………..Eliminates yeast
Lachesis mutus HPUS……………………….Constipation
Phosphoricum acidum HPUS………………..Nausea
Phytolacca decandra HPUS…………………Itching skin
Pulsatilla HPUS……………………………….Stomach pain
Sticta pulmonaria HPUS……………………..Shooting pains
Sulphur HPUS………………………………....Itching, burning skin
Thuja occidentalis HPUS………………….….Fungus growths

Uses

for the temporary relief of symptoms commonly associated with candida overgrowth, including:

- fatigue
- headaches
- congestion
- indigestion

Warnings

Ask a doctor before use if:

- you are taking any other medications
- you have a medical condition

When using this product use only as directed

Stop use and ask a doctor if symptoms persist or worsen.

PREGNANCY OR BREAST FEEDING

If pregnant or breast-feeding, ask a health professional before use.

Keep out of the reach of children.

Directions

Dispense Candidol directly into mouth, or add recommended dosage into 8-12 oz. of purified (non-chlorinated) water and drink. Safe for ages 2 and up.

DOSAGE BY WEIGHT

30-50 lbs 1/2 mL
(13.6-22.6 kg) twice per day
50+ lbs 1 mL
(22.6+ kg) twice per day

External Use: If needed, apply to affected areas 2-6 tiems daily until symptoms improve.

Other information

- do not use if tamper seal is broken
- store in a cool, dry place
- product must not come in contact with metal
- do not store next to electrical devices or appliances

Inactive ingredients

citric acid, potassium sorbate, purified ionized mineral water.

Questions or comments?

You can email us at info@hellolife.net or call us toll-free at 1.800.875.0850 Monday through Friday, 9am-5pm ET.

DESCRIPTION

- 30-day supply
- dropper included
- Candidol is made without alcohol or sugar. No gluten added.
  Mftd for: HelloLife, LLC
  4460 44th St. Ste C-600
  Grand Rapids, MI 49512

FDA Pharmaceutical Establishment #1053442, #3009727070
www.candidol.com

Principal Display Panel

NDC 49726-005-02

CANDIDOL®

Candida Overgrowth Symptom Relief

For the temporary relief of symptoms commonly associated with candida overgrowth, including:

- fatigue
- headach
- congestion
- indigestion

2 fl oz (59 mL)

Homeopathic (OTC) Medicine